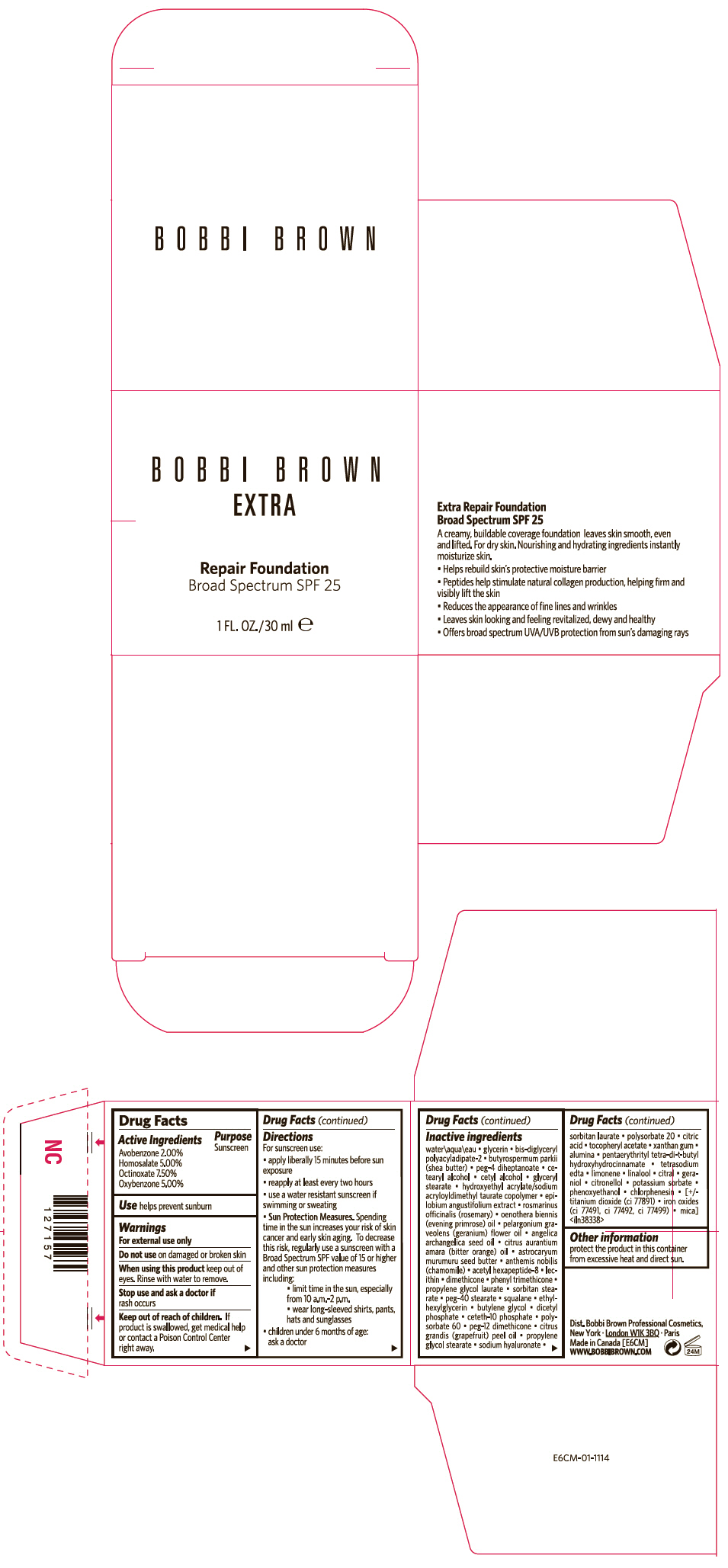 DRUG LABEL: BOBBI BROWN EXTRA 
NDC: 64141-015 | Form: CREAM
Manufacturer: Bobbi Brown Professional Cosmetics Inc.
Category: otc | Type: HUMAN OTC DRUG LABEL
Date: 20210812

ACTIVE INGREDIENTS: OCTINOXATE 0.0821 g/1 mL; HOMOSALATE 0.0548 g/1 mL; OXYBENZONE 0.0548 g/1 mL; AVOBENZONE 0.0219 g/1 mL
INACTIVE INGREDIENTS: WATER; GLYCERIN; SHEA BUTTER; PEG-4 DIHEPTANOATE; CETOSTEARYL ALCOHOL; CETYL ALCOHOL; GLYCERYL MONOSTEARATE; ROSEMARY; EVENING PRIMROSE OIL; PELARGONIUM GRAVEOLENS FLOWER OIL; ANGELICA SEED OIL; CITRUS AURANTIUM FRUIT; ASTROCARYUM MURUMURU SEED BUTTER; CHAMOMILE; ACETYL HEXAPEPTIDE-8; DIMETHICONE; PHENYL TRIMETHICONE; PROPYLENE GLYCOL MONOLAURATE; SORBITAN MONOSTEARATE; PEG-40 STEARATE; SQUALANE; ETHYLHEXYLGLYCERIN; BUTYLENE GLYCOL; DIHEXADECYL PHOSPHATE; CETETH-10 PHOSPHATE; POLYSORBATE 60; CITRUS MAXIMA FRUIT RIND OIL; PROPYLENE GLYCOL MONOSTEARATE; HYALURONATE SODIUM; SORBITAN MONOLAURATE; POLYSORBATE 20; CITRIC ACID MONOHYDRATE; .ALPHA.-TOCOPHEROL ACETATE; XANTHAN GUM; ALUMINUM OXIDE; PENTAERYTHRITOL TETRAKIS(3-(3,5-DI-TERT-BUTYL-4-HYDROXYPHENYL)PROPIONATE); EDETATE SODIUM; LINALOOL, (+/-)-; CITRAL; GERANIOL; .BETA.-CITRONELLOL, (R)-; POTASSIUM SORBATE; PHENOXYETHANOL; CHLORPHENESIN; TITANIUM DIOXIDE; FERRIC OXIDE RED; FERRIC OXIDE YELLOW; FERROSOFERRIC OXIDE; MICA

BOBBI BROWN EXTRA
REPAIR FOUNDATION BROAD SPECTRUM SPF 25

Drug Facts

Active Ingredients

Avobenzone 2.00%
Homosalate 5.00%
Octinoxate 7.50%
Oxybenzone 5.00%

Purpose

Sunscreen

Use

helps prevent sunburn

Warnings

For external use only

Do not use on damaged or broken skin

When using this product keep out of eyes. Rinse with water to remove.

Stop use and ask a doctor if rash occurs

Keep out of reach of children. If product is swallowed, get medical help or contact a Poison Control Center right away.

Directions

For sunscreen use:

- apply liberally 15 minutes before sun exposure
- reapply at least every two hours
- use a water resistant sunscreen if swimming or sweating
- Sun Protection Measures. Spending time in the sun increases your risk of skin cancer and early skin aging. To decrease this risk, regularly use a sunscreen with a Broad Spectrum SPF value of 15 or higher and other sun protection measures including:
  - limit time in the sun, especially from 10 a.m.–2 p.m.
  - wear long-sleeved shirts, pants, hats and sunglasses
- children under 6 months of age: ask a doctor

Inactive ingredients

water\aqua\eau ▪ glycerin ▪ bis-diglyceryl polyacyladipate-2 ▪ butyrospermum parkii (shea butter) ▪ peg-4 diheptanoate ▪ cetearyl alcohol ▪ cetyl alcohol ▪ glyceryl stearate ▪ hydroxyethyl acrylate/sodium acryloyldimethyl taurate copolymer ▪ epilobium angustifolium extract ▪ rosmarinus officinalis (rosemary) ▪ oenothera biennis (evening primrose) oil ▪ pelargonium graveolens (geranium) flower oil ▪ angelica archangelica seed oil ▪ citrus aurantium amara (bitter orange) oil ▪ astrocaryum murumuru seed butter ▪ anthemis nobilis (chamomile) ▪ acetyl hexapeptide-8 ▪ lecithin ▪ dimethicone ▪ phenyl trimethicone ▪ propylene glycol laurate ▪ sorbitan stearate ▪ peg-40 stearate ▪ squalane ▪ ethylhexylglycerin ▪ butylene glycol ▪ dicetyl phosphate ▪ ceteth-10 phosphate ▪ polysorbate 60 ▪ peg-12 dimethicone ▪ citrus grandis (grapefruit) peel oil ▪ propylene glycol stearate ▪ sodium hyaluronate ▪ sorbitan laurate ▪ polysorbate 20 ▪ citric acid ▪ tocopheryl acetate ▪ xanthan gum ▪ alumina ▪ pentaerythrityl tetra-di-t-butyl hydroxyhydrocinnamate ▪ tetrasodium edta ▪ limonene ▪ linalool ▪ citral ▪ geraniol ▪ citronellol ▪ potassium sorbate ▪ phenoxyethanol ▪ chlorphenesin ▪ [+/- titanium dioxide (ci 77891) ▪ iron oxides (ci 77491, ci 77492, ci 77499) ▪ mica] <iln38338>

Other information

protect the product in this container from excessive heat and direct sun.

PRINCIPAL DISPLAY PANEL - 30 ml Jar Carton

BOBBI BROWN
EXTRA

Repair Foundation
Broad Spectrum SPF 25

1 FL. OZ./30 ml e